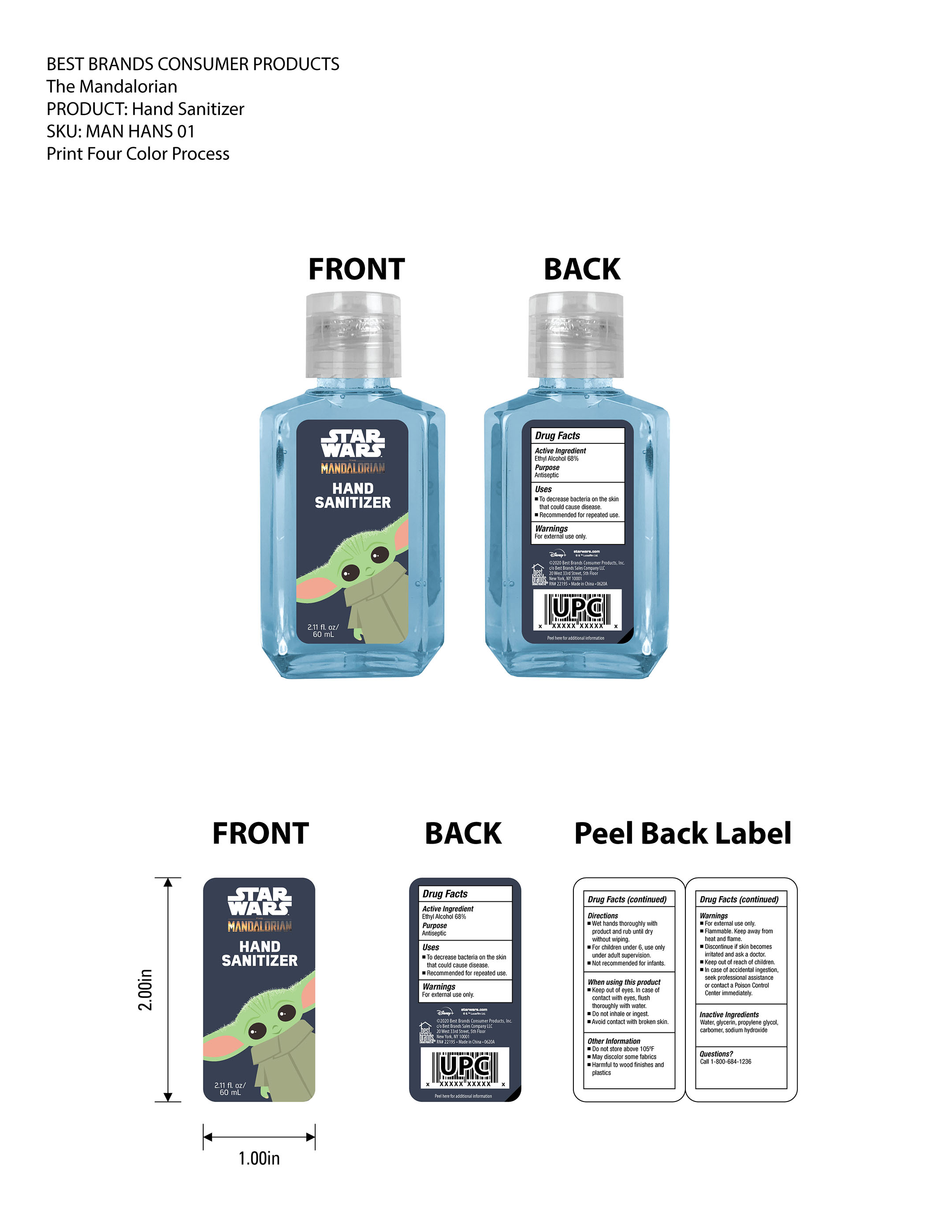 DRUG LABEL: Star War MANDALORIAN Hand Sanitizer
NDC: 74530-002 | Form: SOLUTION
Manufacturer: Best Brand Consumers Products, Inc.
Category: otc | Type: HUMAN OTC DRUG LABEL
Date: 20220102

ACTIVE INGREDIENTS: ALCOHOL 68 mL/100 mL
INACTIVE INGREDIENTS: GLYCERIN; SODIUM HYDROXIDE; WATER; CARBOMER 940; PROPYLENE GLYCOL

Drug Fact

Active Ingredient(s)

Ethyl Alcohol 68%

Purpose

Antiseptic

Use

To decrease the bacteria on the skin that could cause disease

Recommended for repeated use

Warnings

For external use only.

Flammable. Keep away from heat and flame

Discontinue if skin becomes irritated and ask a doctor

WHEN USING

Keep out of eyes. In case of contact with eyes, flush thoroughly with water

Do not inhale or ingest

Avoid contact with broken skin

Keep out of reach of children. In case of accidental ingestion, seek professional assitance or contact a Poison Control Center immediately.

Directions

Wet hands thoroughly with products and rub untill dry withour wiping

For children under 6, use only under adult supervision

Not recommended for infants

Other information

Do not store above 105F

May discolor some fabrics

Harmful to wooden finishes and plastics

Inactive ingredients

Water, glycerin, propylene glycol, carbomer, sodium hydroxide